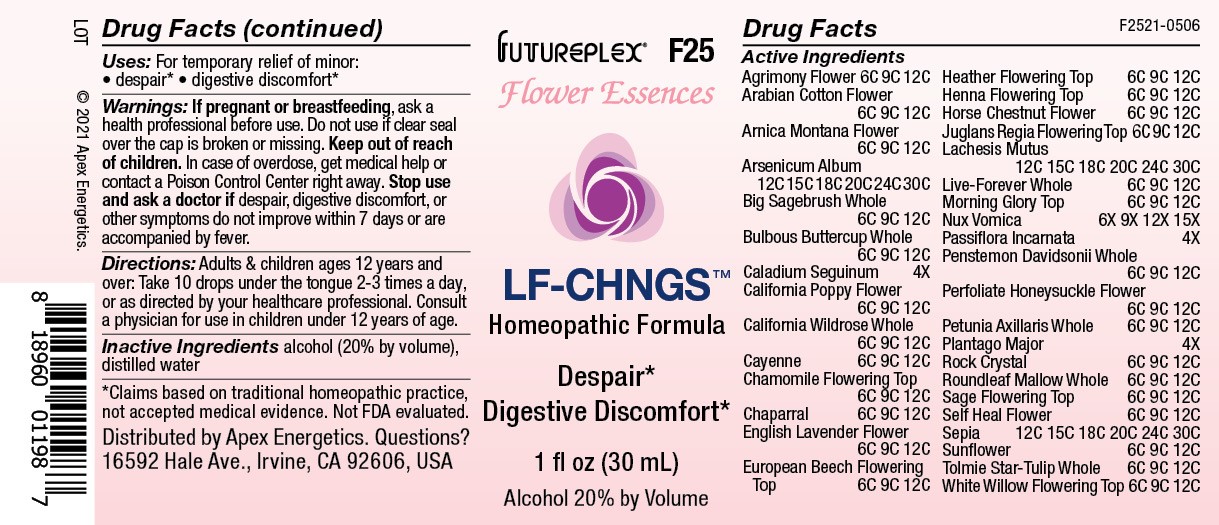 DRUG LABEL: F25
NDC: 63479-0625 | Form: SOLUTION/ DROPS
Manufacturer: Apex Energetics Inc.
Category: homeopathic | Type: HUMAN OTC DRUG LABEL
Date: 20240108

ACTIVE INGREDIENTS: ARSENIC TRIOXIDE 30 [hp_C]/1 mL; LAVANDULA ANGUSTIFOLIA SUBSP. ANGUSTIFOLIA FLOWER 12 [hp_C]/1 mL; SALIX ALBA FLOWERING TOP 12 [hp_C]/1 mL; ARTEMISIA TRIDENTATA WHOLE 12 [hp_C]/1 mL; RANUNCULUS BULBOSUS WHOLE 12 [hp_C]/1 mL; DIEFFENBACHIA SEGUINE 4 [hp_X]/1 mL; ROSA CALIFORNICA WHOLE 12 [hp_C]/1 mL; MATRICARIA CHAMOMILLA FLOWERING TOP 12 [hp_C]/1 mL; AESCULUS HIPPOCASTANUM FLOWER 12 [hp_C]/1 mL; CAPSICUM 12 [hp_C]/1 mL; LARREA TRIDENTATA WHOLE 12 [hp_C]/1 mL; SALVIA OFFICINALIS FLOWERING TOP 12 [hp_C]/1 mL; CALLUNA VULGARIS FLOWERING TOP 12 [hp_C]/1 mL; STRYCHNOS NUX-VOMICA SEED 15 [hp_X]/1 mL; PENSTEMON DAVIDSONII WHOLE 12 [hp_C]/1 mL; LONICERA CAPRIFOLIUM FLOWER 12 [hp_C]/1 mL; GOSSYPIUM HERBACEUM FLOWER 12 [hp_C]/1 mL; ESCHSCHOLZIA CALIFORNICA FLOWER 12 [hp_C]/1 mL; HYLOTELEPHIUM TELEPHIUM WHOLE 12 [hp_C]/1 mL; SEPIA OFFICINALIS JUICE 30 [hp_C]/1 mL; HELIANTHUS ANNUUS FLOWERING TOP 12 [hp_C]/1 mL; CALOCHORTUS TOLMIEI WHOLE 12 [hp_C]/1 mL; LAWSONIA INERMIS FLOWERING TOP 12 [hp_C]/1 mL; AGRIMONIA EUPATORIA FLOWER 12 [hp_C]/1 mL; ARNICA MONTANA FLOWER 12 [hp_C]/1 mL; FAGUS SYLVATICA FLOWERING TOP 12 [hp_C]/1 mL; JUGLANS REGIA FLOWERING TOP 12 [hp_C]/1 mL; LACHESIS MUTA VENOM 30 [hp_C]/1 mL; IPOMOEA PURPUREA TOP 12 [hp_C]/1 mL; PETUNIA AXILLARIS WHOLE 12 [hp_C]/1 mL; PLANTAGO MAJOR 4 [hp_X]/1 mL; SILICON DIOXIDE 12 [hp_C]/1 mL; MALVA NEGLECTA WHOLE 12 [hp_C]/1 mL; PRUNELLA VULGARIS FLOWER 12 [hp_C]/1 mL; PASSIFLORA INCARNATA FLOWERING TOP 4 [hp_X]/1 mL
INACTIVE INGREDIENTS: ALCOHOL; WATER

F25

Active Ingredients
Agrimony Flower | 6C 9C 12C
Arabian Cotton Flower | 6C 9C 12C
Arnica Montana Flower | 6C 9C 12C
Arsenicum Album | 12C 15C 18C 20C 24C 30C
Big Sagebrush Whole | 6C 9C 12C
Bulbous Buttercup Whole | 6C 9C 12C
Caladium Seguinum | 4X
California Poppy Flower | 6C 9C 12C
California Wildrose Whole | 6C 9C 12C
Cayenne | 6C 9C 12C
Chamomile Flowering Top | 6C 9C 12C
Chaparral | 6C 9C 12C
English Lavender Flower | 6C 9C 12C
European Beech Flowering Top | 6C 9C 12C
Heather Flowering Top | 6C 9C 12C
Henna Flowering Top | 6C 9C 12C
Horse Chestnut Flower | 6C 9C 12C
Juglans Regia Flowering Top | 6C 9C 12C
Lachesis Mutus | 12C 15C 18C 20C 24C 30C
Live-Forever Whole | 6C 9C 12C
Morning Glory Top | 6C 9C 12C
Nux Vomica | 6X 9X 12X 15X
Passiflora Incarnata | 4X
Penstemon Davidsonii Whole | 6C 9C 12C
Perfoliate Honeysuckle Flower | 6C 9C 12C
Petunia Axillaris Whole | 6C 9C 12C
Plantago Major | 4X
Rock Crystal | 6C 9C 12C
Roundleaf Mallow Whole | 6C 9C 12C
Sage Flowering Top | 6C 9C 12C
Self Heal Flower | 6C 9C 12C
Sepia | 12C 15C 18C 20C 24C 30C
Sunflower | 6C 9C 12C
Tolmie Star-Tulip Whole | 6C 9C 12C
White Willow Flowering Top | 6C 9C 12C

INDICATIONS AND USAGE

Uses:

For temporary relief of minor:

despair*

digestive discomfort*

*Claims based on traditional homeopathic practice, not accepted medical evidence. Not FDA evaluated.

Warnings:

PREGNANCY OR BREAST FEEDING

If pregnant or breastfeeding, ask a health professional before use.

Do not use if clear seal over the cap is broken or missing.

Keep out of reach of children. In case of overdose, get medical help or contact a Poison Control Center right away.

Stop use and ask a doctor if despair, digestive discomfort, or other symptoms do not improve within 7 days or are accompanied by fever.

Directions:

Adults & children ages 12 years and over: Take 5-10 drops under the tongue 2-3 times a day, or as directed by your healthcare professional. Consult a physician for use in children under 12 years of age.

Inactive Ingredients

alcohol (20% by volume), distilled water

Distributed by Apex Energetics. Questions?

16592 Hale Ave., Irvine, CA 92606, USA

PACKAGE LABEL

FUTUREPLEX® F25

Flower Essences

LF-CHNGS™

Homeopathic Formula

Despair*
Digestive Discomfort *

1 fl oz (30 mL)

Alcohol 20% by Volume